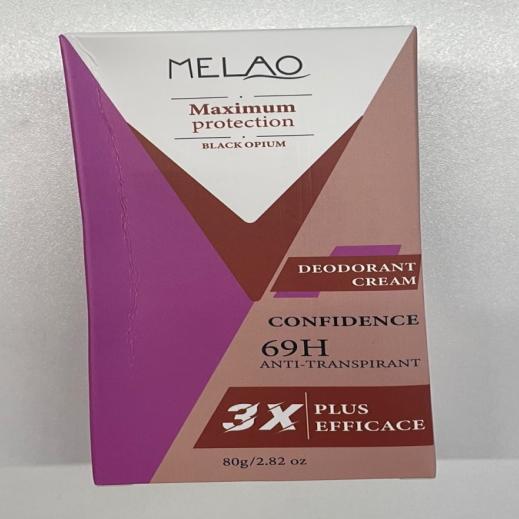 DRUG LABEL: MELAO DEODORANT Cream
NDC: 83566-582 | Form: CREAM
Manufacturer: Guangzhou Yilong Cosmetics Co., Ltd
Category: otc | Type: HUMAN OTC DRUG LABEL
Date: 20240820

ACTIVE INGREDIENTS: PHENOXYETHANOL 0.37 g/100 g
INACTIVE INGREDIENTS: GLYCERIN 3 g/100 g; SAURURUS CHINENSIS WHOLE 0.5 g/100 g; 2-HYDROXYPROPYL METHACRYLATE 0.55 g/100 g; TARAXACUM OFFICINALE LEAF 0.5 g/100 g; PENTAMETHYL CYCLOPENTASILOXANE 4.6 g/100 g; ISOHEXADECANE 1.8 g/100 g; MODIFIED CORN STARCH (1-OCTENYL SUCCINIC ANHYDRIDE) 0.52 g/100 g; DISODIUM EDTA-COPPER 0.08 g/100 g; PARFUMIDINE 0.01 g/100 g; COCOS NUCIFERA WHOLE 1.4 g/100 g; POLYSORBATE 60 1.2 g/100 g; PEG-20 GLYCERYL STEARATE 0.65 g/100 g; LITHIUM SILICATE 1 g/100 g; WATER O-15 58 g/100 g; PYRETHRUM EXTRACT 0.5 g/100 g; ETHYLHEXYLGLYCERIN 0.14 g/100 g; ALUMINUM CHLOROHYDRATE 15 g/100 g; ETHYLHEXYL PALMITATE 5 g/100 g; STEPHANIA TETRANDRA ROOT 0.4 g/100 g; PEG-100 STEARATE 0.58 g/100 g; CETEARYL BEHENATE 2.7 g/100 g; SQUALANE 2 g/100 g

MELAO DEODORANT CREAM

Active ingredients

Phenoxyethanol 0.37%

Inactive ingredients

Water 58%

Aluminum Chlorohydrate 15%

Ethylhexyl Palmitate 5%

Cyclopentasiloxane 4.6%

Glycerin 3%

Cetearyl Alcohol 2.7%

Squalane 2%

lsohexadecane 1.8%

Cocos Nucifera (Coconut) Oil 1.4%

Polysorbate 60 1.2%

Silica 1%

Glyceryl Stearate 0.65%

PEG-100 Stearate 0.58%

Hydroxypropyl Methylcellulose 0.55%

Corn Starch Modified 0.52%

Saururus Chinensis Leaf/Root Extract 0.5%

Taraxacum Officinale (Dandelion) Leaf

Extract 0.5%

Stephania Tetrandra Root Extract 0.4%

Ethylhexylglycerin 0.14%

Disodium EDTA 0.08%

Parfum 0.01%

Purpose

Deodorization

Uses

STEP1: Clean and thoroughly dry your skin.

STEP2: Twist the bottom of the product.

STEP3: Gently apply to the underarms or other desired areas.

Warning

For external use only.

Stop use and ask a doctor if

rash occurs.

Do not use

on damaged or broken skin.

When using this product

keep out of eyes. Rinse withwater to remove.

Keep out of reach of children.

If swallowed, get medical help or contact a Poison Control Center right away.

DOSAGE & ADMINISTRATION

Squeeze out an appropriate amount of product and spread evenly on skin.